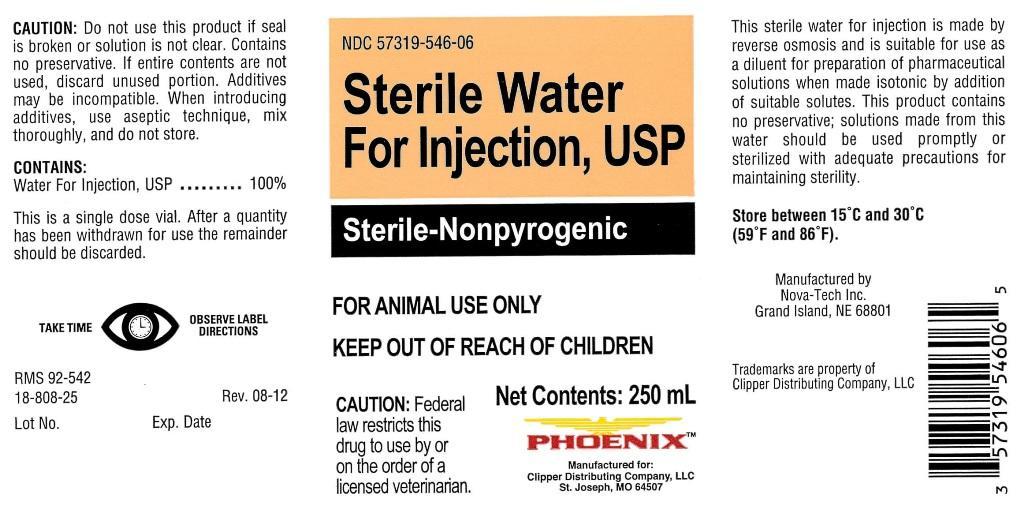 DRUG LABEL: Sterile Water
NDC: 57319-546 | Form: INJECTION
Manufacturer: Clipper
Category: animal | Type: PRESCRIPTION ANIMAL DRUG LABEL
Date: 20140512

ACTIVE INGREDIENTS: WATER 250 mL/250 mL

Sterile Water For Injection, USP

CAUTION:

Do not use this product if seal is broken or solution is not clear. Contains no preservative. If entire contents are not used, discard unused portion. Additives may be incompatible. When introducing additives, use aseptic technique, mix thoroughly, and do not store.

CONTAINS:

Water For Injection, USP.................100%

This is a single dose vial. After a quantity has been withdrawn for use the remainder should be discarded.

GENERAL PRECAUTIONS

TAKE TIME OBSERVE LABEL DIRECTIONS

INFORMATION FOR OWNERS/CAREGIVERS

RMS 92-542

18-808-25

Rev. 08-12

Lot No.

Exp. Date

GENERAL PRECAUTIONS

Sterile-Nonpyrogenic

FOR ANIMAL USE ONLY

KEEP OUT OF REACH OF CHILDREN

CAUTION:

Federal law restricts this drug to use by or on the order of a licensed veterinarian.

INDICATIONS AND USAGE

This sterile water for injection is made by reverse osmosis and is suitable for use as a diluent for preparation of pharmaceutical solutions when made isotonic by addition of suitable solutes. This product contains no preservative; solutions made from this water should be used promptly or sterilized with adequate precautions for maintaining sterility.

STORAGE AND HANDLING

Store between 15 degrees C and 30 degrees C (59 degrees F and 86 degrees F).

INFORMATION FOR OWNERS/CAREGIVERS

Manufactured by

Nova-Tech, Inc.

Grand Island, NE 68801

Trademarks are property of Clipper Distributing Company, LLC